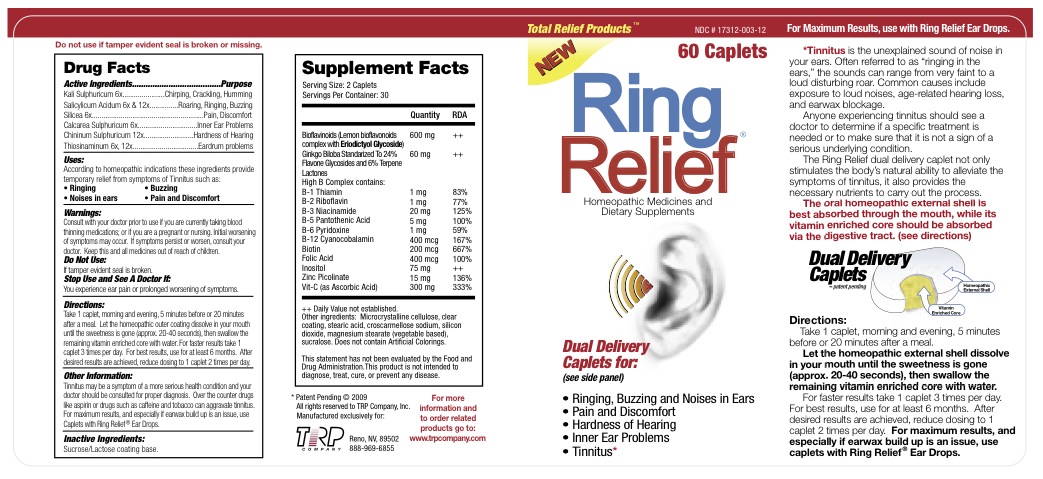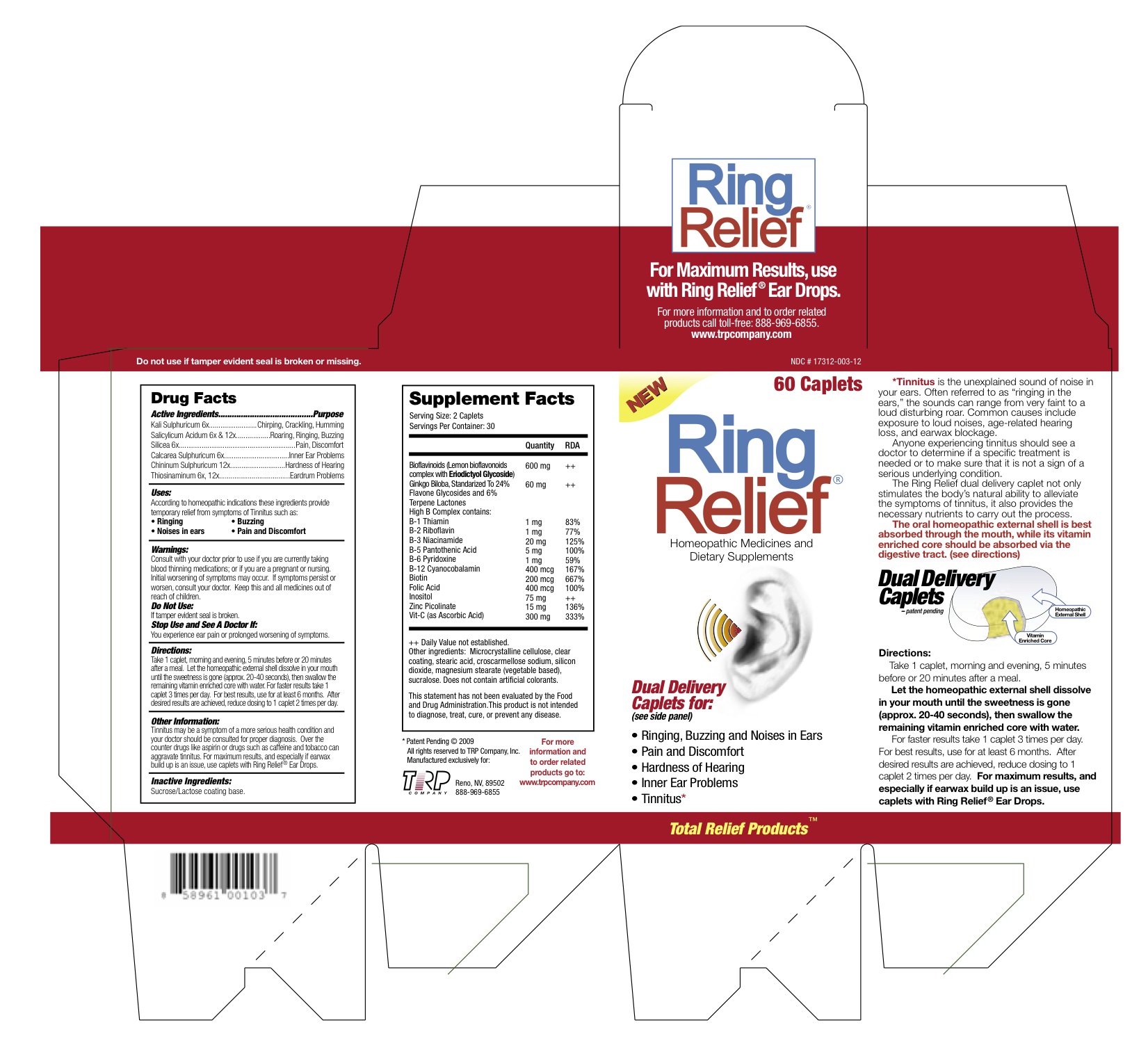 DRUG LABEL: Ring Relief
NDC: 17312-003 | Form: Tablet, Multilayer
Manufacturer: TRP Company
Category: homeopathic | Type: HUMAN OTC DRUG LABEL
Date: 20120531

ACTIVE INGREDIENTS: Potassium Sulfate 6 [hp_X]/1 1; Salicylic Acid 6 [hp_X]/1 1; Silicon Dioxide 6 [hp_X]/1 1; Calcium Sulfate Anhydrous 6 [hp_X]/1 1; Quinine Sulfate 12 [hp_X]/1 1; Allylthiourea 6 [hp_X]/1 1; Citrus Bioflavonoids 300 mg/1 1; Ginkgo 30 mg/1 1; Thiamine 0.5 mg/1 1; Riboflavin 0.5 mg/1 1; Niacinamide 10 mg/1 1; Pantothenic Acid 2.5 mg/1 1; Pyridoxine 0.5 mg/1 1; Cyanocobalamin 200 ug/1 1; Biotin 100 ug/1 1; Folic Acid 200 ug/1 1; Inositol 37.5 mg/1 1; Zinc Picolinate 7.5 mg/1 1; Ascorbic Acid 150 mg/1 1
INACTIVE INGREDIENTS: Sucrose; Lactose; Cellulose, Microcrystalline; Stearic Acid; Croscarmellose Sodium; Silicon Dioxide; Magnesium Stearate; Sucralose

Ring Relief

Homeopathic Purpose

Kali Sulphuricum | 6x | Chirping, Crackling, Humming
Salicylicum Acidum | 6x,12x | Roaring, Ringing, Buzzing
Silicea | 6x | Pain, Discomfort
Calcarea Sulphuricum | 6x | Inner Ear Problems
Chininum Sulphuricum | 12x | Hardness of Hearing
Thiosinaminum | 6x,12x | Eardrum Problems

Active Ingredients

Kali Sulphuricum | 6x
Salicylicum Acidum | 6x,12x
Silicea | 6x
Calcarea Sulphuricum | 6x
Chininum Sulphuricum | 12x
Thiosinaminum | 6x,12x
Citrus Bioflavonoids | 300 mg
Ginkgo | 30 mg
Thiamine | 0.5 mg
Riboflavin | 0.5 mg
Niacinamide | 10 mg
Pantothenic Acid | 2.5 mg
Pyridoxine | 0.5 mg
Cyanocobalamin | 200 mcg
Biotin | 100 mcg
Folic Acid | 200 mcg
Inositol | 37.5 mg
Zinc Picolinate | 7.5 mg
Ascorbic Acid | 150 mg

Inactive Ingredients

Sucrose

Lactose

Microcrystalline cellulose

Clear coating

Stearic Acid

Croscarmellose Sodium

Silicon Dioxide

Magnesium Stearate

Sucralose

Uses

According to homeopathic indications these ingredients provide temporary relief from symptoms of Tinnitus such as:
- Ringing
- Buzzing
- Noises in ears
- Pain and Discomfort

Warnings

- Consult with your doctor prior to use if you are currently taking blood thinning medications or if you are a pregnant or nursing.
- Initial worsening of symptoms may occur.
- If symptoms persist or worsen, consult your doctor.

KEEP OUT OF REACH OF CHILDREN

Keep this and all medicines out of reach of children.

Do not use

If tamper evident seal is broken.

Stop Use and See A Doctor If

You experience ear pain or prolonged worsening of symptoms.

Directions

Take 1 caplet, morning and evening, 5 minutes before or 20 minutes after a meal. Let the homeopathic external shell dissolve in your mouth until the sweetness is gone (approx. 20-40 seconds), then swallow the remaining vitamin enriched core with water. For faster results take 1 caplet 3 times per day. For best results, use for at least 6 months. After desired results are achieved, reduce dosing to 1 caplet 2 times per day.

Other Information

Tinnitus may be a symptom of a more serious health condition and your doctor should be consulted for proper diagnosis. Over the counter drugs like aspirin or drugs such as caffeine and tobacco can aggravate tinnitus. For maximum results, and especially if earwax build up is an issue, use caplets with Ring Relief Ear Drops.

QUESTIONS

TRP Company
1575 Delucchi Lane #115
Reno, NV 89502
888-969-6855
www.trpcompany.com